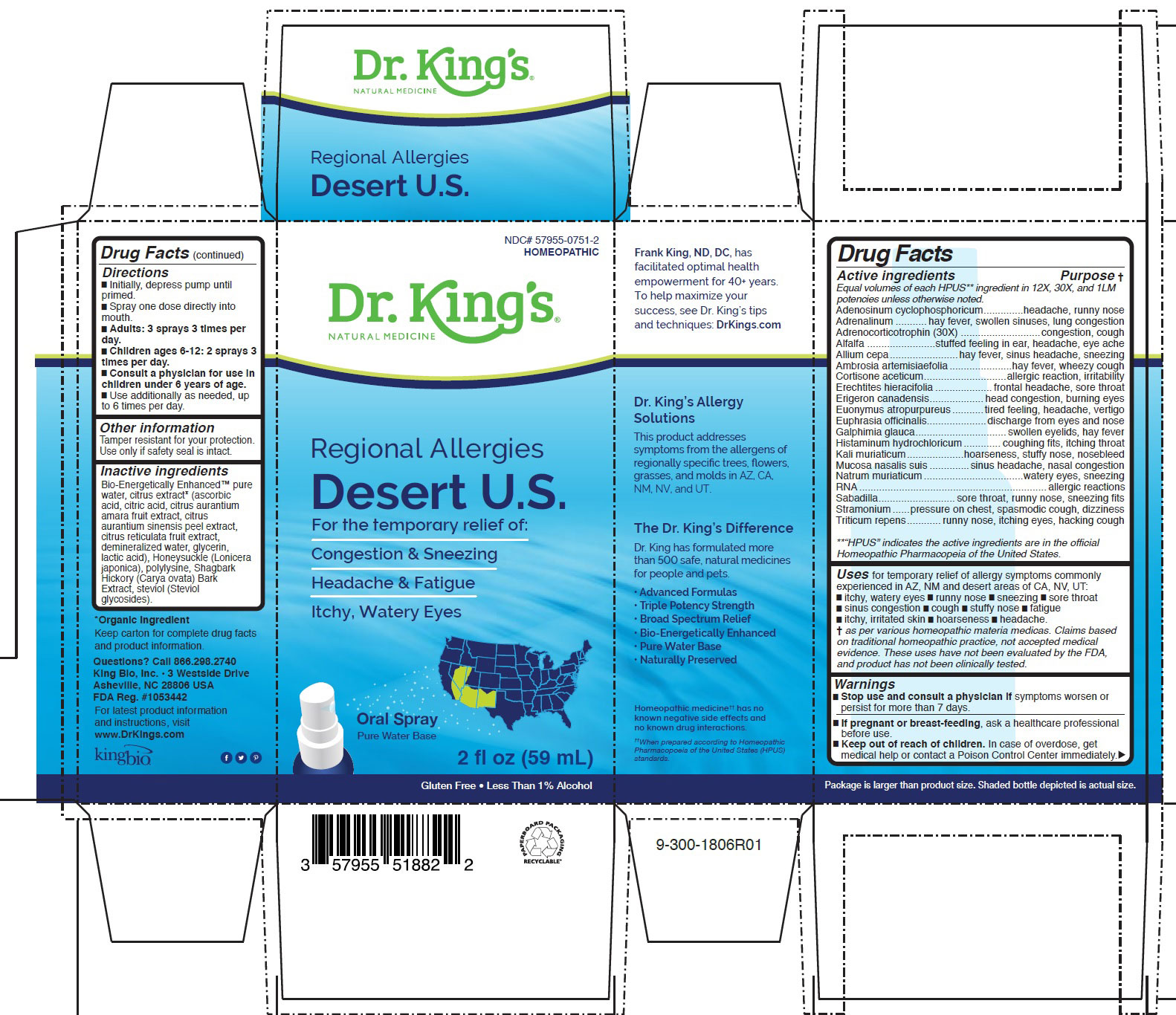 DRUG LABEL: Regional Allergies Desert U.S.
NDC: 57955-0751 | Form: LIQUID
Manufacturer: King Bio Inc.
Category: homeopathic | Type: HUMAN OTC DRUG LABEL
Date: 20200706

ACTIVE INGREDIENTS: ADENOSINE CYCLIC PHOSPHATE 12 [hp_X]/59 mL; EPINEPHRINE 12 [hp_X]/59 mL; CORTICOTROPIN 12 [hp_X]/59 mL; ALFALFA 12 [hp_X]/59 mL; ONION 12 [hp_X]/59 mL; AMBROSIA ARTEMISIIFOLIA 12 [hp_X]/59 mL; CORTISONE ACETATE 12 [hp_X]/59 mL; ERECHTITES HIERACIIFOLIUS 12 [hp_X]/59 mL; CONYZA CANADENSIS 12 [hp_X]/59 mL; EUONYMUS ATROPURPUREUS BRANCH BARK/ROOT BARK 12 [hp_X]/59 mL; EUPHRASIA STRICTA 12 [hp_X]/59 mL; GALPHIMIA GLAUCA FLOWERING TOP 12 [hp_X]/59 mL; HISTAMINE DIHYDROCHLORIDE 12 [hp_X]/59 mL; POTASSIUM CHLORIDE 12 [hp_X]/59 mL; SUS SCROFA NASAL MUCOSA 12 [hp_X]/59 mL; SODIUM CHLORIDE 12 [hp_X]/59 mL; SACCHAROMYCES CEREVISIAE RNA 12 [hp_X]/59 mL; SCHOENOCAULON OFFICINALE SEED 12 [hp_X]/59 mL; DATURA STRAMONIUM 12 [hp_X]/59 mL; ELYMUS REPENS ROOT 12 [hp_X]/59 mL
INACTIVE INGREDIENTS: WATER; CITRIC ACID MONOHYDRATE; POTASSIUM SORBATE; LONICERA CAPRIFOLIUM FLOWER; POLY-L-LYSINE (30000-70000 MW); CARYA OVATA BARK; STEVIOL

Regional Allergies Desert U.S.

ACTIVE INGREDIENT

Drug Facts___________________________________________________________________________________________________________

HPUS active ingredients: Adenosinum cyclophosphoricum, Adrenalinum, Adrenocorticotrophin, Alfalfa, Allium cepa, Ambrosia artemisiaefolia, Cortisone aceticum, Erechtites hieracifolia, Erigeron canadensis, Euonymus atropurpureus, Euphrasia officinalis, Galphimia glauca, Histaminum hydrochloricum, Kali muriaticum, Mucosa nasalis suis, Natrum muriaticum, RNA, Sabadilla, Stramonium and Triticum repens.

INDICATIONS AND USAGE

Uses for temporary relief of allergy symptoms commonly experienced in AZ, NM and desert areas of CA, NV, UT.

- itchy, watery eyes
- runny nose
- sneezing
- sore throat
- sinus congestion
- cough
- stuff nose
- fatigue
- itchy, irritated skin
- hoarseness
- headache

Directions

- Initially depress pump until primed.
- Spray one dose directly into mouth.
- Adults: 3 sprays 3 times per day.
- Children ages 6-12: 2 sprays 3 times per day.
- Use additionally as needed, up to 6 times per day.

Warnings

Stop use and consult a physician if symptoms worsen or persist for more than 7 days.

PREGNANCY OR BREAST FEEDING

If pregnant or breast-feeding, ask a healthcare professional before use.

Keep out of reach of children. In case of overdose, get medical help or contact a Poison Control Center immediately.

Inactive ingredients

Bio-Energetically Enhanced™ pure
water, citrus extract* (ascorbic
acid, citric acid, citrus aurantium
amara fruit extract, citrus
aurantium sinensis peel extract,
citrus reticulata fruit extract,
demineralized water, glycerin,
lactic acid), Honeysuckle (Lonicera
japonica), polylysine, Shagbark
Hickory (Carya ovata) Bark
Extract, steviol (Steviol
glycosides).

PURPOSE

Drug Facts___________________________________________________________________________________________________________

HPUS active ingredients Purpose

Equal volumes of each ingredient in 12X, 30X, and LM1 potencies.

Adenosinum cyclophosphoricum.........................................headache, runny nose

Adrenalinum....................................................................hay fever, swollen sinuses, lung congestion

Adrenocorticorticotrophin..................................................inflammation, congestion, cough

Alfalfa............................................................................stuffed feeling in ear, headache, eye ache

Allium cepa.....................................................................hay fever, sinus headache, sneezing

Ambrosia artemisiaefolia...................................................hay fever, wheezy cough

Cortisone aceticum...........................................................allergic reaction, irritability

Erechtites hieracifolia........................................................frontal headache, sore throat

Erigeron canadensis..........................................................head congestion, burning eyes

Euonymus atropurpureus...................................................tired feeling, headache, vertigo

Euphrasia officinalis...........................................................discharge from eyes and nose

Galphimia glauca...............................................................swollen eyelids, hay fever

Histaminum hydrochloricum................................................coughing fits, itching throat

Kali muriaticum.................................................................hoarseness, stuffy nose, nosebleed

Mucosa nasalis suis............................................................sinus headache, nasal congestion

Natrum muriaticum............................................................watery eyes, sneezing

RNA.................................................................................allergic reactions

Sabadilla..........................................................................sore throat, runny nose, sneezing fits

Stramonium......................................................................pressure on chest, spasmodic cough, dizziness

Triticum repens..................................................................runny nose, itching eyes, hacking cough

STORAGE AND HANDLING

Keep carton for complete drug facts
and product information.

Questions? Call 866.298.2740
King Bio, Inc. • 3 Westside Drive
Asheville, NC 28806 USA
FDA Reg. #1053442

For latest product information
and instructions, visit
www.DrKings.com